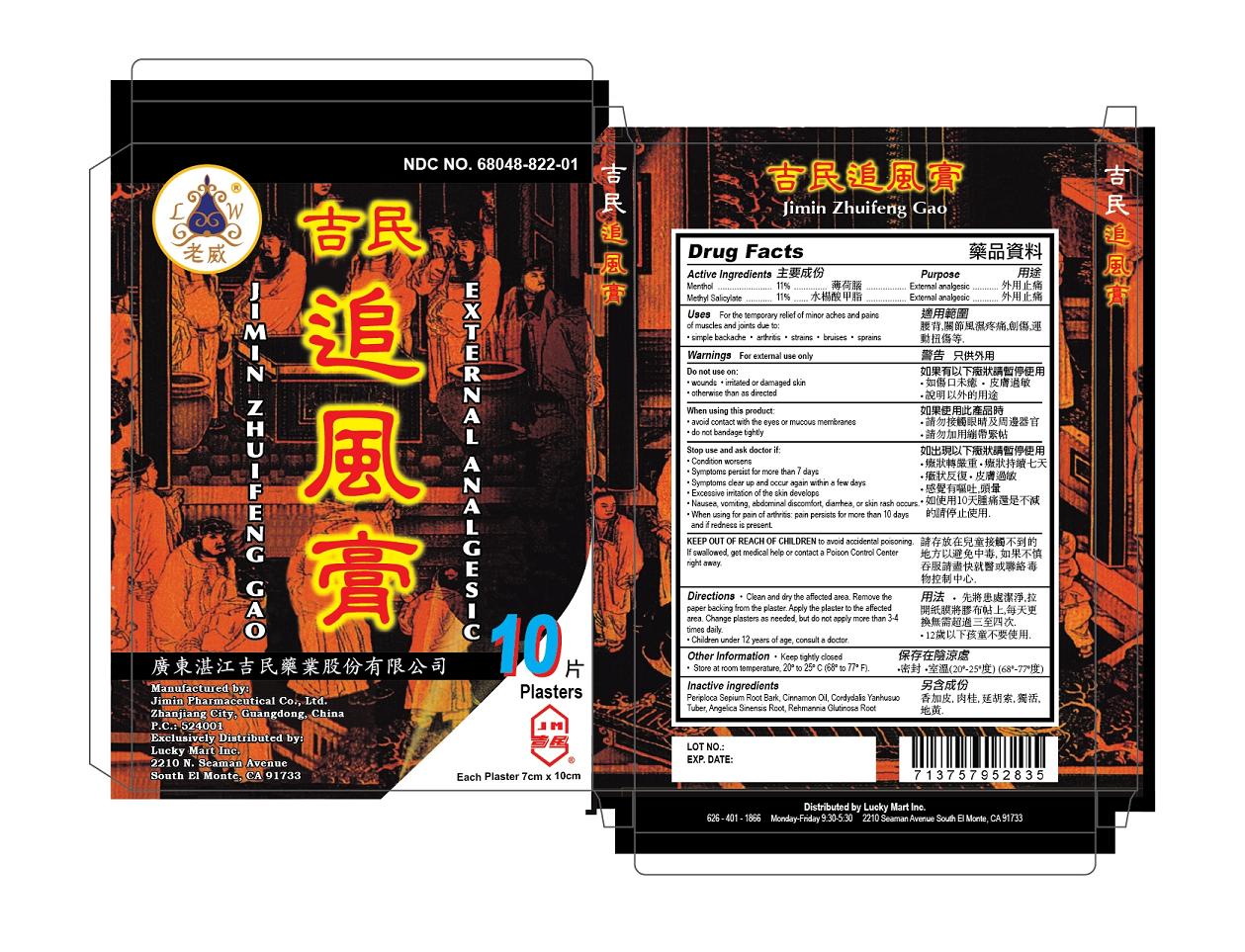 DRUG LABEL: Jimin Zhuifeng Gao
NDC: 68048-822 | Form: PLASTER
Manufacturer: Guangdong Zhanjiang Jimin Pharmaceutical Co. Ltd
Category: otc | Type: HUMAN OTC DRUG LABEL
Date: 20140619

ACTIVE INGREDIENTS: MENTHOL 9 g/100 g; METHYL SALICYLATE 9 g/100 g
INACTIVE INGREDIENTS: PERIPLOCA SEPIUM ROOT BARK; CINNAMON OIL; CORYDALIS YANHUSUO TUBER; ANGELICA SINENSIS ROOT; REHMANNIA GLUTINOSA ROOT

Guangdong Zhanjiang Jimin Pharmaceutical Co, Ltd

Active Ingredients

Menthol 11%

Methyl Salicylate 11%

Purpose

Menthol External Analgesic

Methyl Salicylate External Analgesic

Uses

For the temporary relief of minor aches and pains of muscles and joints due to:

Simple backache, arthristis, strains, bruises, sprains.

Warnings

For external use only.

Do not use

On wounds, on irritated or damaged skin, otherwise than as directed.

When using this product

Avoid contact with the eyes or mucous membranes.

Do not bandage tightly.

Stop use and ask a doctor if

Condition worsens.

Symptoms persist for more than 7 days.

Symptoms clear up and occur again within a few days.

Excessive irritation of the skin develops.

Nausea, vomitting, abdominal discomfort, diarrhea or skin rash occurs.

When using for pain of arthristis: pain persists for more than 10 days and if redness is present.

Keep out of reach of children to avoid accidental poisoning. If swallowed, get medical help or contact a Poison Control Center right away.

Directions

Adults and children 3 years of age and older, clean and dry the affected area, remove the paper backing from th plaste. Apply the plaster to the affected area. Change plasters as needed, but do not apply more than 3 to 4 times daily.

Children under 12 years of age: contact a doctor.

Other Information

Keep tightly closed.

Store at room temperature, 20 to 25 degrees centigrade (68-77 degrees Farenheit)

Inactive Ingredients

PERIPLOCA SEPIUM ROOT BARK, CINNAMON OIL, CORYDALIS YANHUSUO TUBER, ANGELICA SINENSIS ROOTANGELICA, REHMANNIA GLUTINOSA ROOT